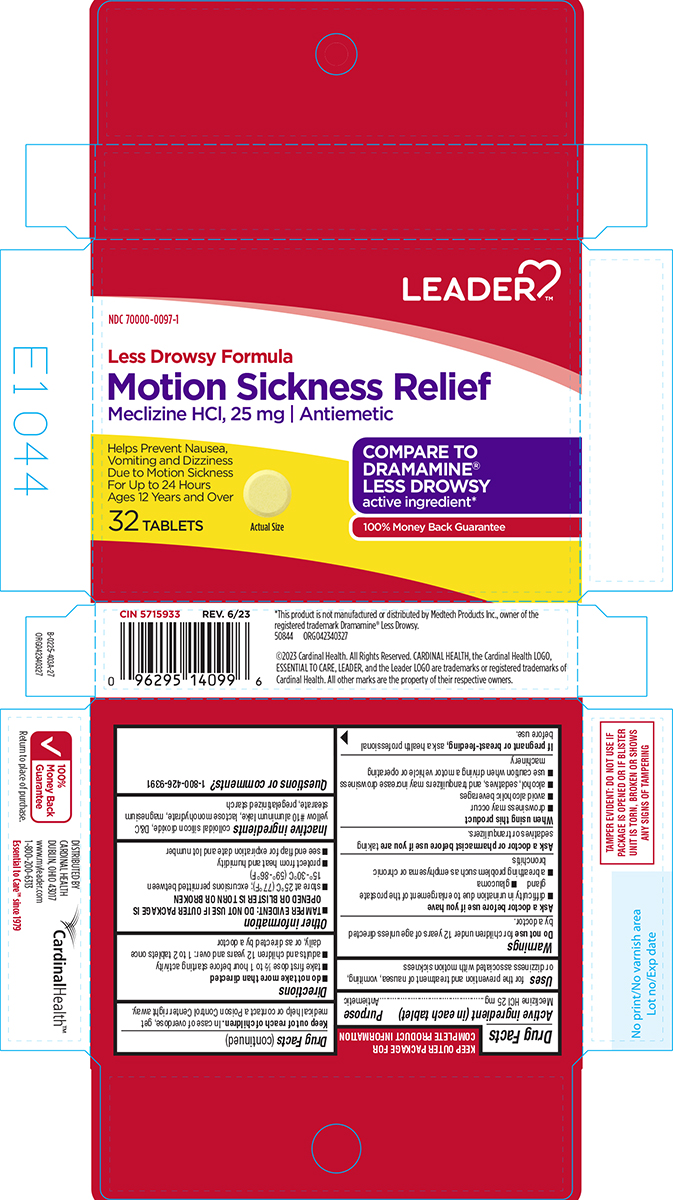 DRUG LABEL: Motion Sickness Relief
NDC: 70000-0097 | Form: TABLET
Manufacturer: Cardinal Health 110, LLC. DBA Leader
Category: otc | Type: HUMAN OTC DRUG LABEL
Date: 20250607

ACTIVE INGREDIENTS: MECLIZINE HYDROCHLORIDE 25 mg/1 1
INACTIVE INGREDIENTS: SILICON DIOXIDE; D&C YELLOW NO. 10 ALUMINUM LAKE; LACTOSE MONOHYDRATE; MAGNESIUM STEARATE; STARCH, CORN

Leader 44-403

Active ingredient (in each tablet)

Meclizine HCl 25 mg

Purpose

Antiemetic

Uses

for the prevention and treatment of nausea, vomiting, or dizziness associated with motion sickness

Warnings

Do not use

for children under 12 years of age unless directed by a doctor.

Ask a doctor before use if you have

- difficulty in urination due to enlargement of the prostate gland
- glaucoma
- a breathing problem such as emphysema or chronic bronchitis

Ask a doctor or pharmacist before use if you are

taking sedatives or tranquilizers.

When using this product

- drowsiness may occur
- avoid alcoholic beverages
- alcohol, sedatives, and tranquilizers may increase drowsiness
- use caution when driving a motor vehicle or operating machinery

If pregnant or breast-feeding,

ask a health professional before use.

Keep out of reach of children.

In case of overdose, get medical help or contact a Poison Control Center right away.

Directions

- do not take more than directed
- take first dose ½ to 1 hour before starting activity
- adults and children 12 years and over: 1 to 2 tablets once daily, or as directed by a doctor

Other information

- TAMPER EVIDENT: DO NOT USE IF OUTER PACKAGE IS OPENED OR BLISTER IS TORN OR BROKEN
- store at 25°C (77°F); excursions permitted between 15°-30°C (59°-86°F)
- protect from heat and humidity
- see end flap for expiration date and lot number

Inactive ingredients

colloidal silicon dioxide, D&C yellow #10 aluminum lake, lactose monohydrate, magnesium stearate, pregelatinized starch

Questions or comments?

1-800-426-9391

Principal display panel

LEADER™

NDC 70000-0097-1

Less Drowsy Formula
Motion Sickness Relief
Meclizine HCI, 25 mg | Antiemetic

Helps Prevent Nausea,
Vomiting and Dizziness
Due to Motion Sickness
For Up to 24 Hours
Ages 12 Years and Over

COMPARE TO
DRAMAMINE®
LESS DROWSY
active ingredient*

100% Money Back Guarantee

32 TABLETS

Actual Size

TAMPER EVIDENT: DO NOT USE IF
PACKAGE IS OPENED OR IF BLISTER
UNIT IS TORN, BROKEN OR SHOWS
ANY SIGNS OF TAMPERING

*This product is not manufactured or distributed by Medtech Products Inc., owner of the
registered trademark Dramamine® Less Drowsy.
50844 ORG042340327

©2023 Cardinal Health. All Rights Reserved. CARDINAL HEALTH, the Cardinal Health LOGO,
ESSENTIAL TO CARE, LEADER, and the Leader LOGO are trademarks or registered trademarks of
Cardinal Health. All other marks are the property of their respective owners.

DISTRIBUTED BY
CARDINAL HEALTH
DUBLIN, OHIO 43017
www.myleader.com
1-800-200-6313
Essential to Care™ since 1979

100%
Money Back
Guarantee

Return to place of purchase.

Leader 44-403A